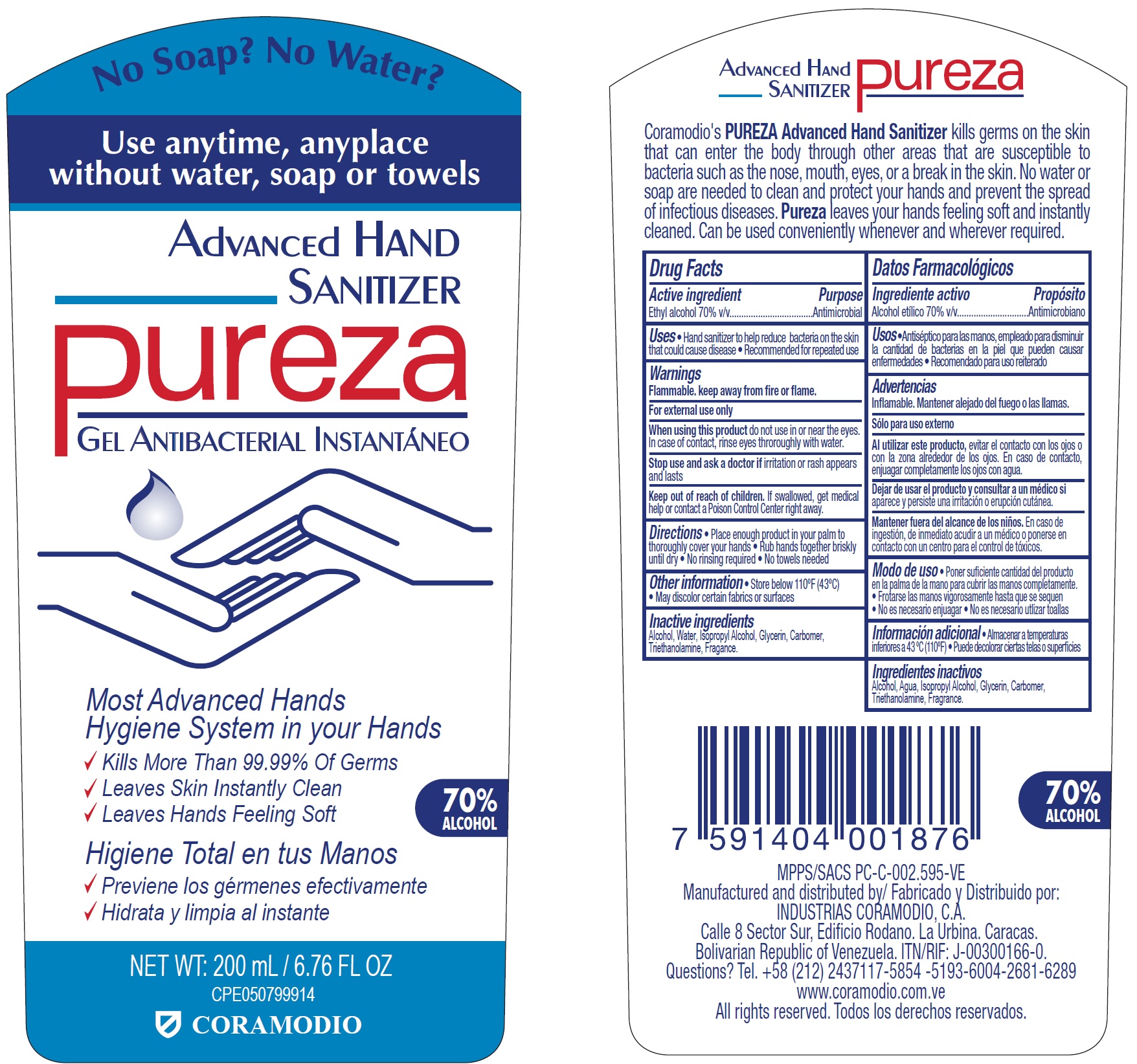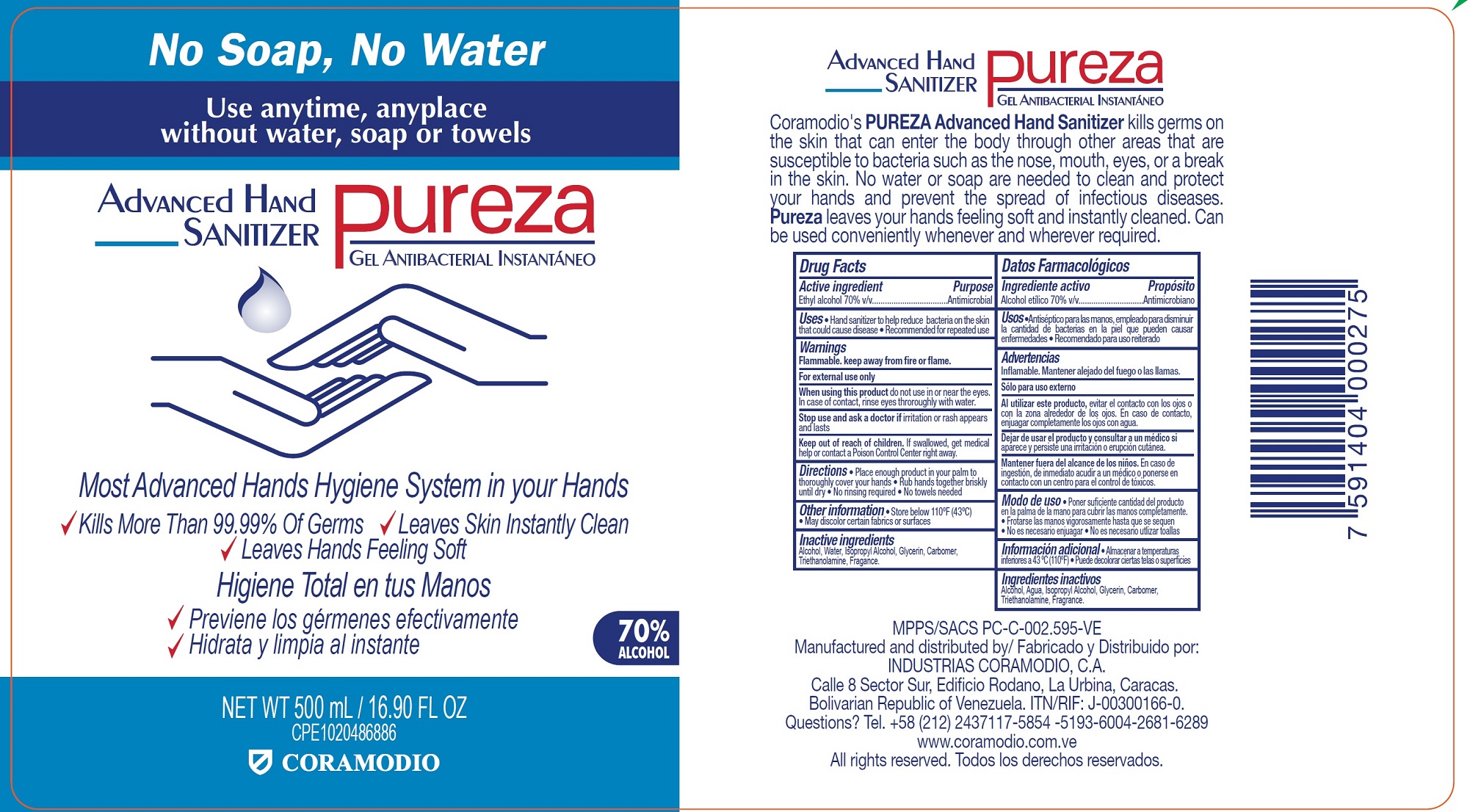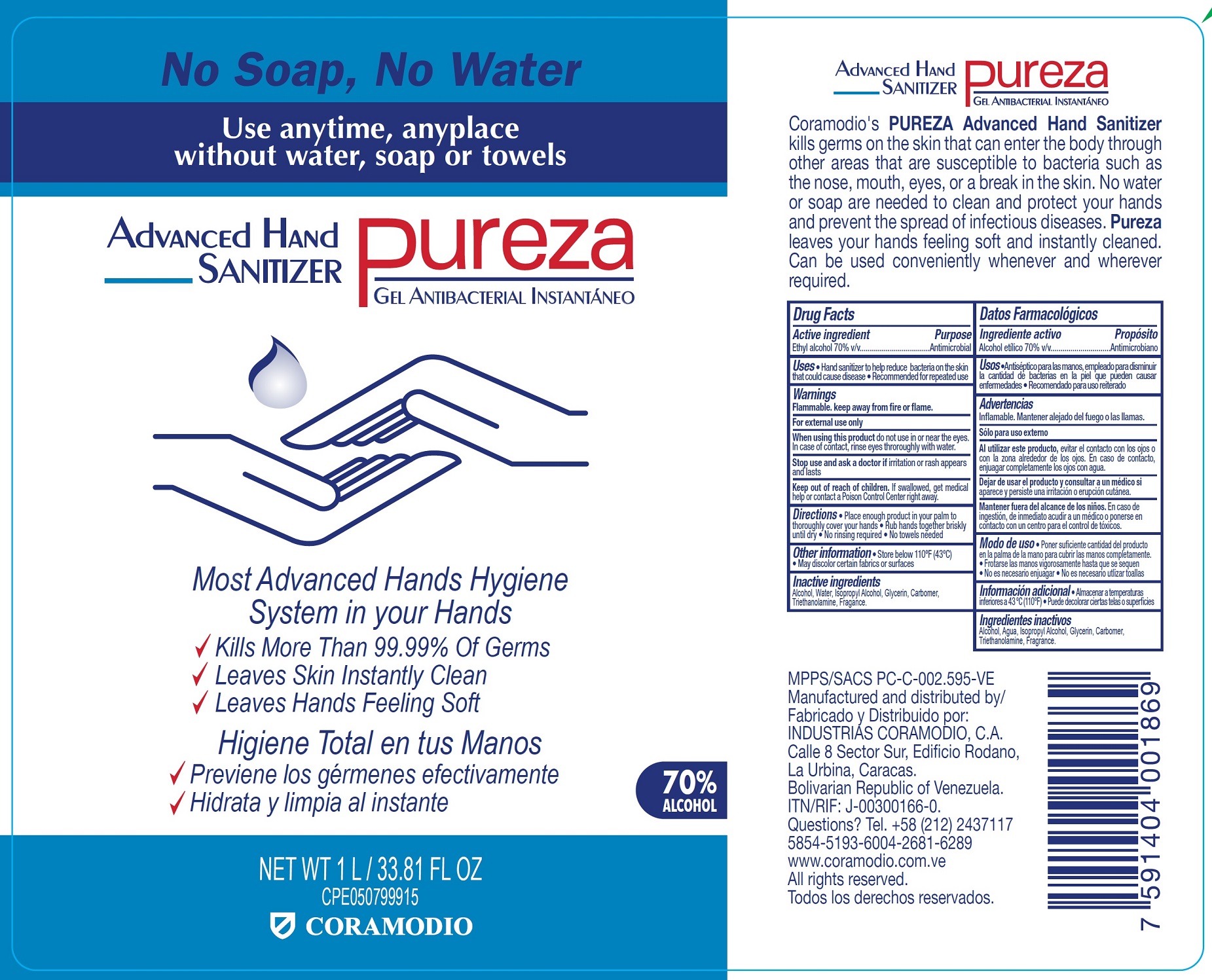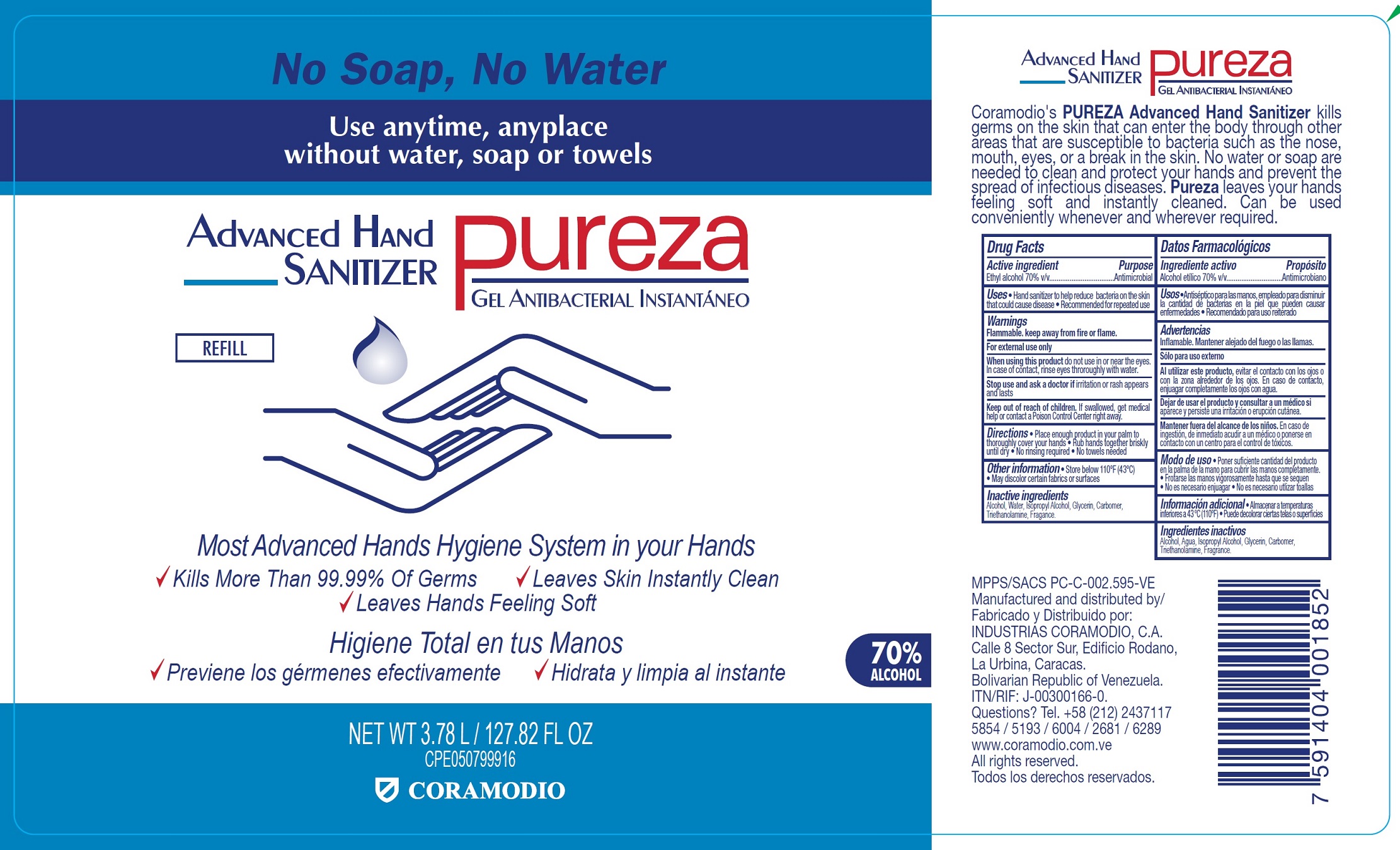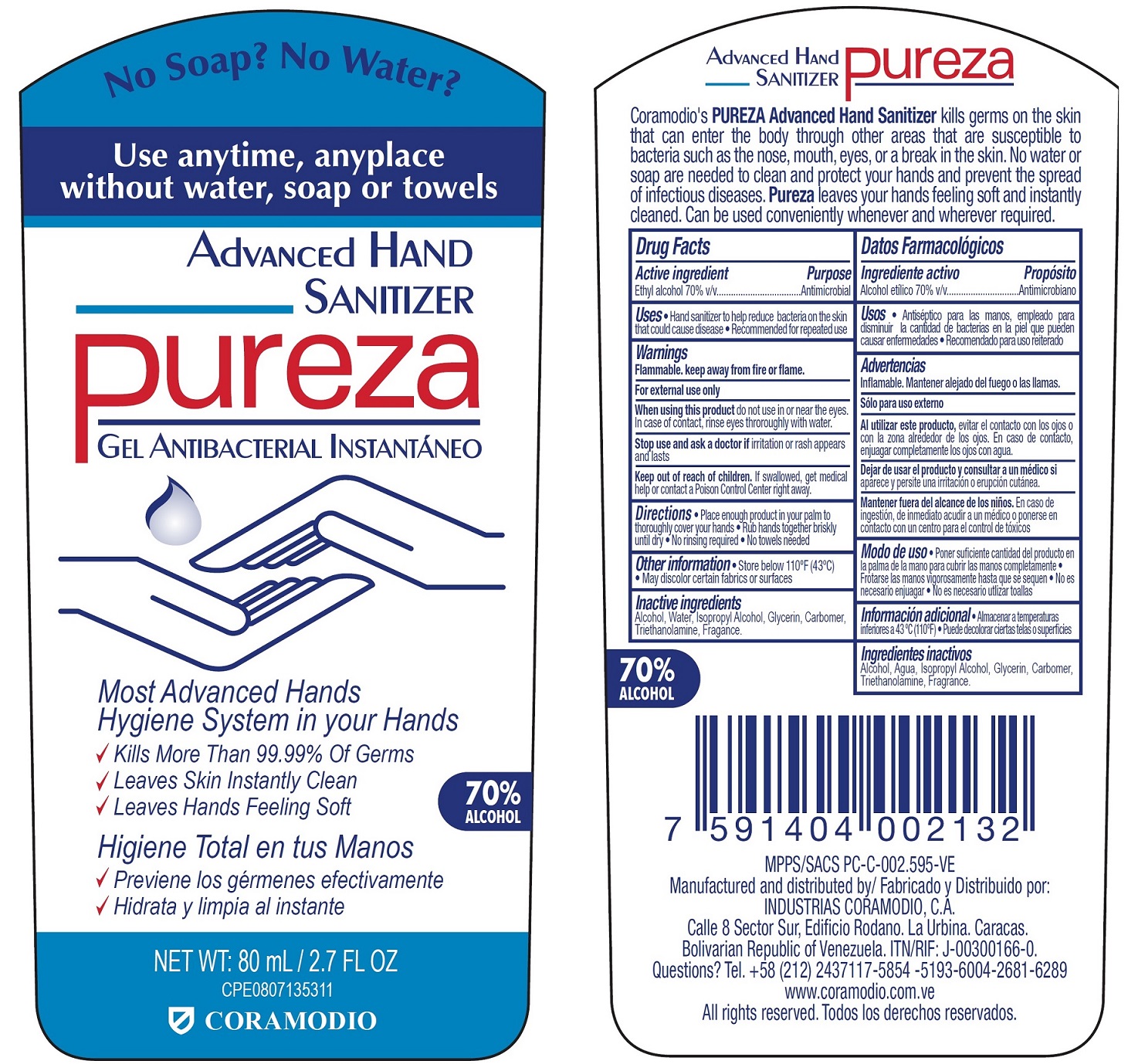 DRUG LABEL: Pureza Advanced Hand Sanitizer
NDC: 81182-000 | Form: GEL
Manufacturer: Industrias Coramodio C.A
Category: otc | Type: HUMAN OTC DRUG LABEL
Date: 20201207

ACTIVE INGREDIENTS: ALCOHOL 0.7 mL/1 mL
INACTIVE INGREDIENTS: WATER; ISOPROPYL ALCOHOL; GLYCERIN; CARBOMER HOMOPOLYMER, UNSPECIFIED TYPE; TROLAMINE

Pureza Advanced Hand Sanitizer

Active ingredient

Ethyl alcohol 70% v/v

Purpose

Antimicrobial

Uses

- Hand sanitizer to help reduce bacteria on the skin that could cause disease
- Recommended for repeated use

Warnings

Flammable. keep away from fire or flame.
For external use only

When using this product

do not use in or near the eyes. In case of contact, rinse eyes throroughly with water.

Stop use and ask a doctor if

irritation or rash appears os ojos con agua. and lasts

Keep out of reach of children.

If swallowed, get medical help or contact a Poison Control Center right away.

Directions

• Place enough product in your palm to thoroughly cover your hands • Rub hands together briskly until dry • No rinsing required • No towels needed

Other information

• Store below 110ºF (43ºC)
• May discolor certain fabrics or surfaces

Inactive ingredients

Alcohol, Water, Isopropyl Alcohol, Glycerin, Carbomer, Triethanolamine, Fragance.